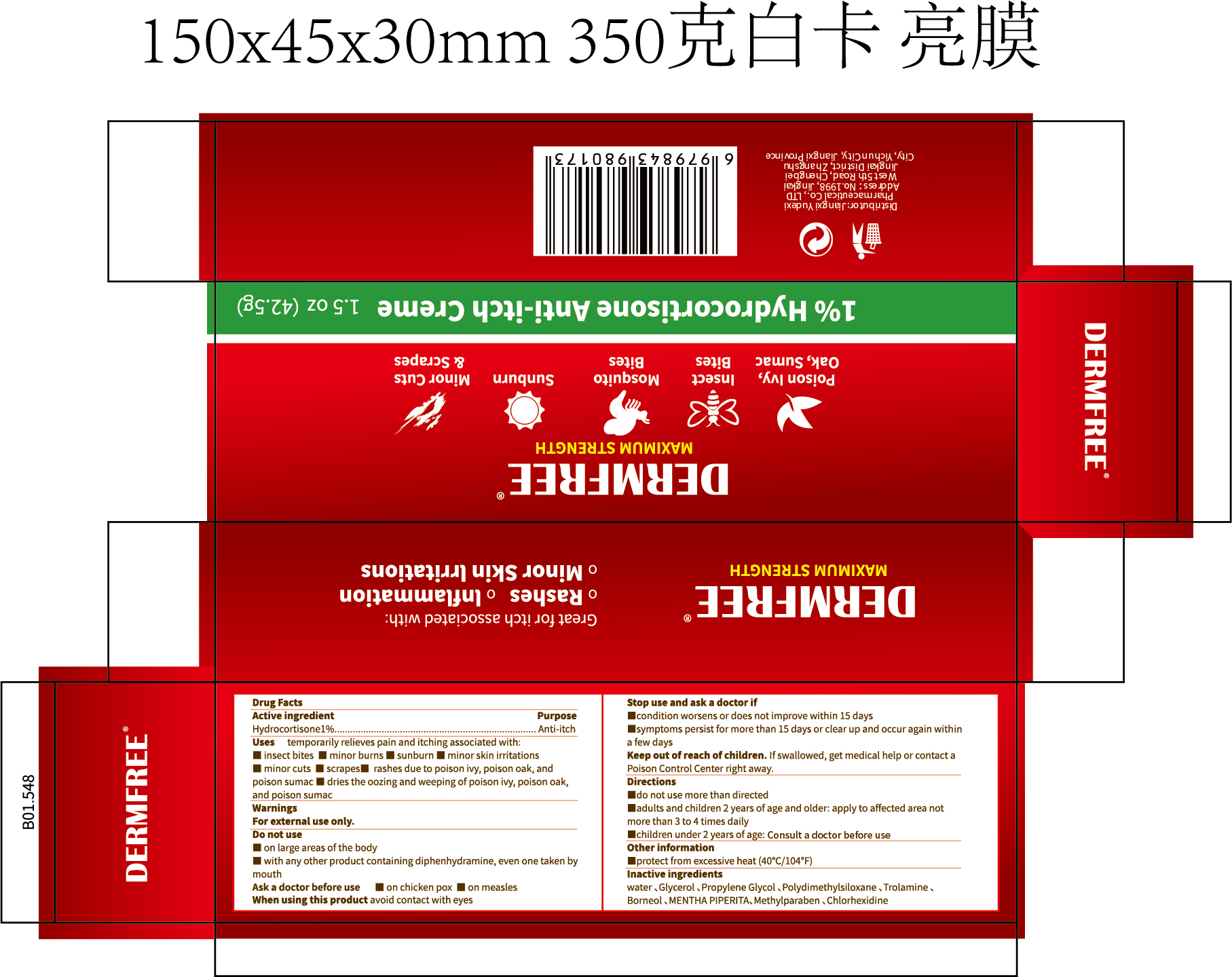 DRUG LABEL: DERMFREE Anti-itch
NDC: 85248-126 | Form: CREAM
Manufacturer: Jiangxi Yudexi Pharmaceutical Co., LTD
Category: otc | Type: HUMAN OTC DRUG LABEL
Date: 20260208

ACTIVE INGREDIENTS: HYDROCORTISONE 1 g/100 g
INACTIVE INGREDIENTS: GLYCERIN; DIMETHICONE; BORNEOL; METHYLPARABEN; CHLORHEXIDINE; TROLAMINE; WATER; PROPYLENE GLYCOL; MENTHA PIPERITA

85248-126

Active Ingredient

Hydrocortisone 1%

Purpose

Anti-itch

Use

temporarily relieves pain and itching associated with:▇insect bites▇ minor burns ▇sunburn▇ minor skin irritations▇ minor cuts ▇scrapes▇ rashes due to poison ivy, poison oak, and poison sumac ▇dries the oozing and weeping of poison ivy, poison oak ，and poison sumac

Warnings

For external use only.

Do not use

▇on large areas of the body ▇with any other product containing diphenhydramine, even one taken bymouth

When Using

avoid contact with eyes

Stop Use

▇condition worsens or does not improve within 15 days ▇symptoms persist for more than 15 days or clear up and occur again within a few days

Ask Doctor

▇on chicken pox ▇ on measles

Keep Oot Of Reach Of Children

If swallowed, get medical help or contact a Poison Control Center right away.

Directions

▇do not use more than directed ▇adults and children 2 years of age and older: apply to affected area not more than 3 to 4 times daily ▇children under 2 years of age: Consult a doctor before use.

Other information

▇protect from excessive heat (40°C/104°F)

Inactive ingredients

water,Glycerol,Propylene Glycol,Polydimethylsiloxane,Trolamine.Borneol,MENTHA PIPERITA, Methylparaben, Chlorhexidine